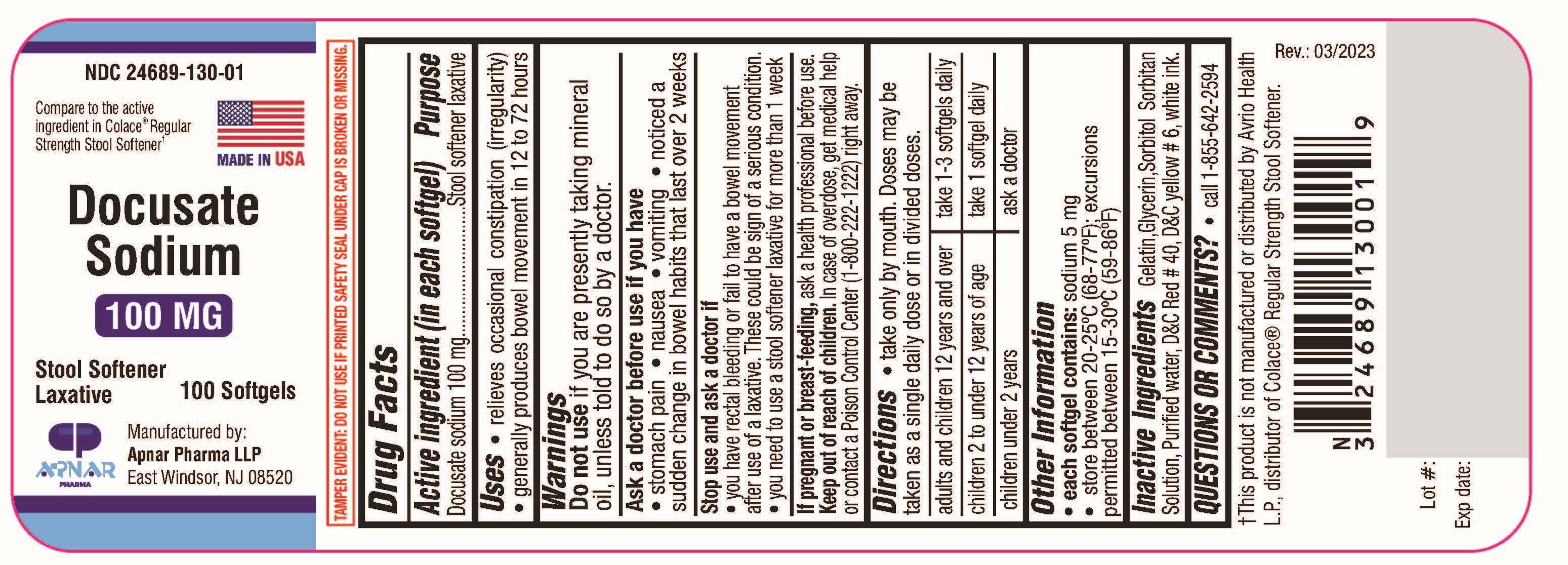 DRUG LABEL: Docusate sodium
NDC: 24689-130 | Form: CAPSULE, LIQUID FILLED
Manufacturer: APNAR PHARMA LP
Category: otc | Type: HUMAN OTC DRUG LABEL
Date: 20250109

ACTIVE INGREDIENTS: DOCUSATE SODIUM 100 mg/1 1
INACTIVE INGREDIENTS: GELATIN; GLYCERIN; SORBITOL; SORBITAN; FD&C YELLOW NO. 6; WATER; FD&C RED NO. 40

DOCUSATE SODIUM SOFTGELS

Active Ingredient (In each softgel)

Docusate Sodium.... 100 mg

Purpose

Stool softener laxative

Uses

- relieves occasional constipation (irregularity)
- generally produces bowel movement in 12 to 72 hours

Warnings

Do not use

if you are presently taking mineral oil, unless told to do so by a doctor.

Ask a doctor before use if you have

- stomach pain
- nausea
- vomiting
- noticed a sudden change in bowel habits that last over 2 weeks

Stop use and ask a doctor if

- you have rectal bleeding or fail to have a bowel movement after use of a laxative. These could be a signs of a serious condition.
- you need to use a stool softner laxative for more than 1 week

If pregnant or breast-feeding,

ask a health professional before use.

Keep out of reach of children.

In case of overdose, get medical help or contact a Poison Control Center (1-800-222-1222) right away.

Directions

take only by mouth. Doses may be taken as a single daily dose or in divided doses.

adults and children 12 years and over : take 1 to 3 softgels daily
children 2 to under 12 years of age : take 1 softgel daily
children under 2 years : ask a doctor

Other Information

each softgel contains: sodium 5 mg
store between 20ºC - 25ºC (68-77ºF);excursions permitted between 15-30ºC (59-86ºF)

INACTIVE INGREDIENT

Gelatin, Glycerin, Sorbitol Sorbitan solution, Purified water , D&C Red #40, D&C Yellow #6, White Ink

Questions or Comments ?

Call 1-855-642-2594

Compare to the active ingredient in Colace® Regular Strength Stool Softener†

†This product is not manufactured or distributed by Avrio Health L.P., distributor of Colace® Regular Strength Stool Softener.

Rev.: 03/2023

Manufactured by:
Apnar Pharma LLP
East Windsor, NJ 08520

PACKAGE LABEL

NDC 24689-130-01

Docusate Sodium 100mg

Stool Softener Laxative

MADE IN USA

100 Softgels